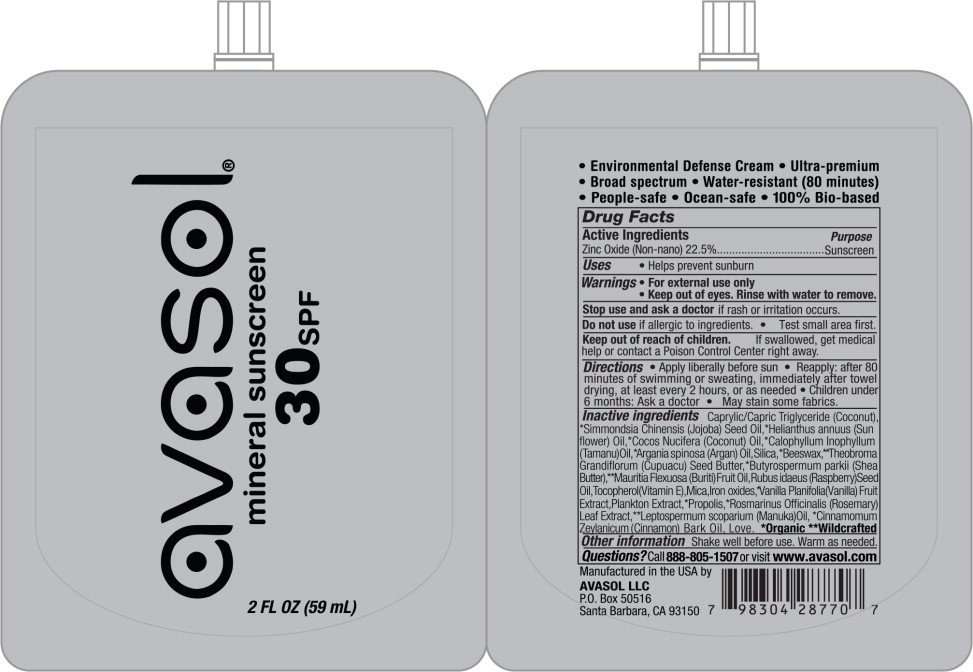 DRUG LABEL: ENVIRONMENTAL DEFENSE
NDC: 58518-010 | Form: CREAM
Manufacturer: Avasol LLC
Category: otc | Type: HUMAN OTC DRUG LABEL
Date: 20260126

ACTIVE INGREDIENTS: ZINC OXIDE 225 mg/100 mL
INACTIVE INGREDIENTS: COCONUT OIL; MEDIUM-CHAIN TRIGLYCERIDES; JOJOBA OIL; SUNFLOWER OIL; TAMANU OIL; ARGAN OIL; SILICON DIOXIDE; YELLOW WAX; THEOBROMA GRANDIFLORUM SEED; SHEANUT; MAURITIA FLEXUOSA WHOLE; RUBUS IDAEUS SEED; TOCOPHEROL; VANILLA BEAN; MICA; HAEMATOCOCCUS PLUVIALIS; FERROUS OXIDE; PROPOLIS WAX; MANUKA OIL; ROSEMARY; CINNAMON BARK OIL

ENVIRONMENTAL DEFENSE- zinc oxide

Active Ingredients

Zinc Oxide (Non-nano) 22.5%

Purpose

Sunscreen

Uses

- Helps prevent sunburn

Warnings

- For external use only
- Keep out of eyes. Rinse with water to remove

Stop use and ask a doctor if rash or irritation occurs.

Do not use if allergic to ingredients.

- Test small area first.

Keep out of reach of children. If swallowed, get medical help or contact a Poison Control Center right away.

Directions

- Apply liberally before sun
- Reapply: after 80 minutes of swimming or sweating, immediately after towel drying, at least every 2 hours, or as needed
- Children under 6 months: Ask a doctor
- May stain some fabrics.

Inactive ingredients

Caprylic/Capric Triglyceride (Coconut), *Simmondsia Chinensis (Jojoba) Seed Oil,*Helianthus annuus (Sun flower) Oil,*Cocos Nucifera (Coconut) Oil,*Calophyllum Inophyllum (Tamanu)Oil,*Argania spinosa (Argan) Oil, Silica, *Beeswax,*Theobroma Grandiflorum (Cupuacu) Seed Butter,*Butyrospermum parkii (Shea Butter),**Mauritia Flexuosa (Buriti) Fruit Oil, Rubus idaeus (Raspberry) Seed Oil, Tocopherol (Vitamin E), Mica, Iron oxides, *Vanilla Planifolia(Vanilla) Fruit Extract, Plankton Extract,*Propolis,*Rosmarinus Officinalis (Rosemary) Leaf Extract,**Leptospermum scoparium (Manuka)Oil, *Cinnamomum Zeylanicum (Cinnamon) Bark Oil, Love. *Organic **Wildcrafted

Other information

Shake well before use. Warm as needed.

Questions?

Call 888-805-1507or visit www.avasol.com

Principal Display Panel - 2 Fl Oz Bottle Label

avasol®

mineral sunscreen

30 SPF

2 FL OZ (59 mL)